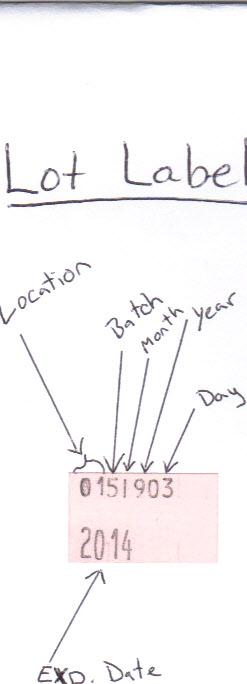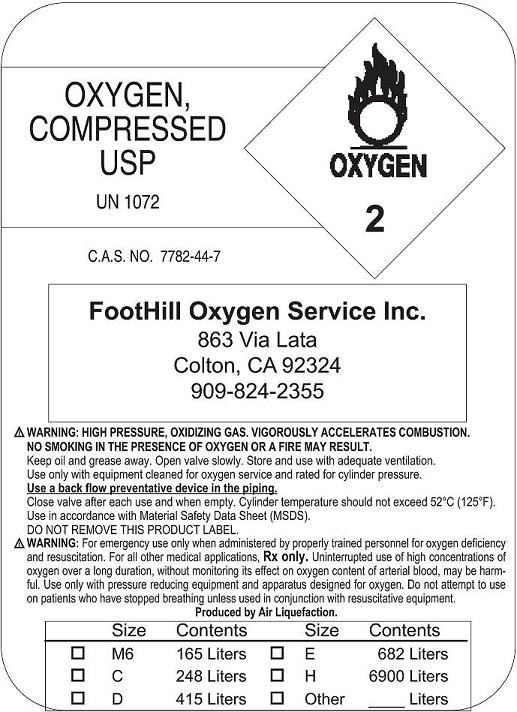 DRUG LABEL: Oxygen
NDC: 64246-0001 | Form: GAS
Manufacturer: Foothill Oxygen Service, Inc.
Category: prescription | Type: HUMAN PRESCRIPTION DRUG LABEL
Date: 20091022

ACTIVE INGREDIENTS: Oxygen 99 L/100 L

Oxygen